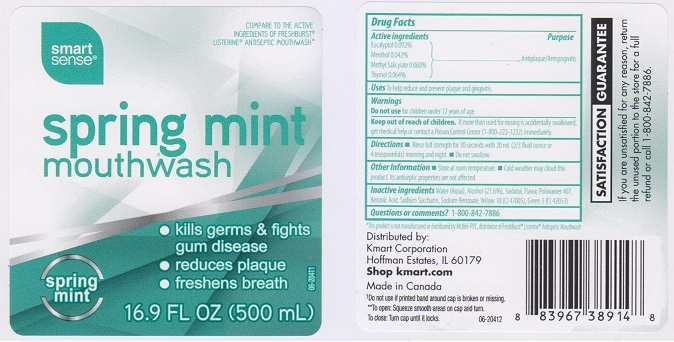 DRUG LABEL: SMART SENSE
NDC: 49738-558 | Form: LIQUID
Manufacturer: KMART CORPORATION
Category: otc | Type: HUMAN OTC DRUG LABEL
Date: 20160309

ACTIVE INGREDIENTS: EUCALYPTOL 0.92 mg/1 mL; MENTHOL 0.42 mg/1 mL; METHYL SALICYLATE 0.6 mg/1 mL; THYMOL 0.64 mg/1 mL
INACTIVE INGREDIENTS: WATER; ALCOHOL; SORBITOL; POLOXAMER 407; BENZOIC ACID; SACCHARIN SODIUM; SODIUM BENZOATE; D&C YELLOW NO. 10; FD&C GREEN NO. 3

DRUG FACTS

Active ingredients

Eucalyptol 0.092%, Menthol 0.042%, Methyl Salicylate 0.060%, Thymol 0.064%

Purpose

Antiplaque/Antigingivitis

Uses

To help reduce and prevent plaque and gingivitis.

Warnings

Do not use for children under 12 years of age.

Keep out of reach of children.

If more than used for rinsing is accidentally swallowed, get medical help or contact a Poison Control Center (1-800-222-1222) immediately.

Directions

- Rinse full strength for 30 seconds with 20 mL (2/3 fluid ounce or 4 teaspoonfuls) morning and night.
- Do not swallow.

Other information

- Store at room temperature.
- Cold weather may cloud this product. Its antiseptic properties are not affected.

Inactive ingredients

Water (Aqua), Alcohol (21.6%), Sorbitol, Flavor, Poloxamer 407, Benzoic Acid, Sodium Saccharin, Sodium Benzoate, Yellow 10 (CI 47005), Green 3 (CI 42053).

Questions or comments?

1-800-842-7886